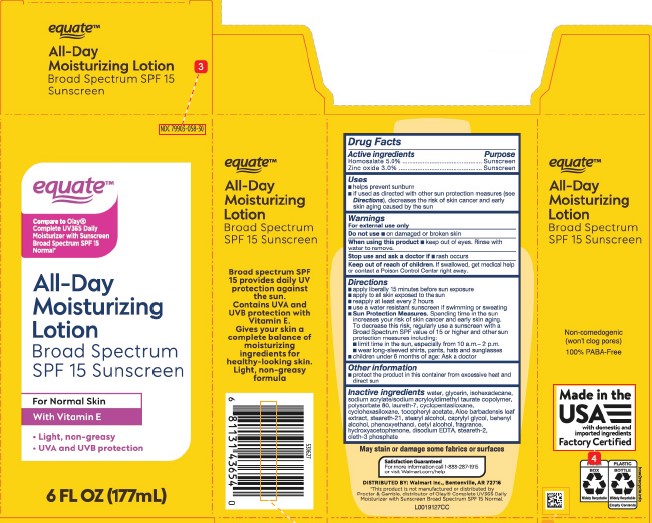 DRUG LABEL: SPF Beauty
NDC: 79903-058 | Form: LOTION
Manufacturer: Walmart Inc.
Category: otc | Type: HUMAN OTC DRUG LABEL
Date: 20260227

ACTIVE INGREDIENTS: HOMOSALATE 50 mg/1 mL; ZINC OXIDE 30 mg/1 mL
INACTIVE INGREDIENTS: WATER; GLYCERIN; ISOHEXADECANE; SODIUM ACRYLATE/SODIUM ACRYLOYLDIMETHYLTAURATE COPOLYMER (4000000 MW); POLYSORBATE 80; LAURETH-7; CYCLOMETHICONE 5; CYCLOMETHICONE 6; .ALPHA.-TOCOPHEROL ACETATE; ALOE VERA LEAF; STEARETH-21; STEARYL ALCOHOL; CAPRYLYL GLYCOL; DOCOSANOL; PHENOXYETHANOL; CETYL ALCOHOL; HYDROXYACETOPHENONE; EDETATE DISODIUM ANHYDROUS; STEARETH-2 PHOSPHATE; OLETH-3 PHOSPHATE

Equate 043.000/043AA
Original Beauty Lotion SPF 15

Active ingredients

Homosalate 5.0%

Zinc oxide 3.0%

Purpose

Sunscreen

Uses

- helps prevent sunburn
- if used as directed with other sun protection measures (see Directions), decreases the rise of skin cancer and early skin aging caused by the sun

Warnings

For external use only

Do not use

on damaged or broken skin

When using this product

- keep out of eyes. Rinse with water to remove.

Stop use and ask a doctor if

- rash occurs

Keep out of reach of children.

If swallowed, get medical help or contact a Poison Control Center right away.

Directions

- apply liberally 15 minutes before sun exposure
- apply to all skin exposed to the sun
- reapply at least every 2 hours
- use a water resistant sunscreen if swimming or sweating
- Sun Protection measures. Spending time in the sun increases your risk of skin cancer and early skin aging. To decrease this risk, regularly use a sunscreen with a Broad spectrum SPF value of 15 or higher and other sun protection measures including:
- limit the time in the sun, especially from 10 a.m. - 2 p.m.
- wear long-sleeved shirts, pants, hats and sunglasses
- children under 6 months of age: ask a doctor

Other information

- Protect the product in this container from excessive heat and direct sun

Inactive ingredients

water, glycerin, isohexadecane, sodium acrylate/sodium acryloyldimethyl taurate copolymer, polysorbate 80, laureth-7, cyclopentasiloxane, cyclohexasiloxane, tocopheryl acetate, Aloe barbadensis leaf extract, steareth-21, stearyl alcohol, caprylyl glycol, behenyl alcohol, phenoxyethanol, cetyl alcohol, fragrance, hydroxyacetophenone, disodium EDTA, steareth-2, oleth-3 phosphate

Claims

May stain or damage some fabrics or surfaces

equate ™

ALL-DAY MOISTURIZING LOTION

Broad Spectrum SPF 15 Sunscreen

Broad spectrum SPF 15 provides daily protection against the sun.

Contains UVA and UVB protection with Vitamin E.

Gives your skin a complete balance of moisturizing ingredients for healthy-looking skin.

Light, non-greasy formula.

Non-comedogenic (won't clog pores)

100% PABA-Free

Made in the USA with domestic and imported ingredients

Factory Certified

PAPER BOX

Widely Recyclable

PLASTIC BOTTLE

Widely Recyclable

Empty Contents

how2recycle.info

ADVERSE REACTION

Satsfaction guaranteed

For more information call 1-888-287-1915 or visit Walmart.com/help

DISTRIBUTED BY: Walmart Inc., Bentonville, AR 72716

Disclaimer

*This product is not manufactured or distributed by Procter & Gamble, distributor of Olay® Complete UV365 Daily Moisturizer with Sunscreen Broad Spectrum SPF 15 Normal.

Principal display panel

equate ™

ALL-DAY MOISTURIZING LOTION

Broad Spectrum SPF 15 Sunscreen

NDC 79903-058-30

equate ™

Compare to Olay® Complete UV365 Daily Moisturizer with Sunscreen Broad Spectrum SPF 15 Normal*

ALL-DAY MOISTURIZING LOTION

Broad Spectrum SPF 15 Sunscreen

For Normal Skin

With Vitamin E

- Light, non-greasy
- UVA and UVB protection

6 FL OZ (177 mL)